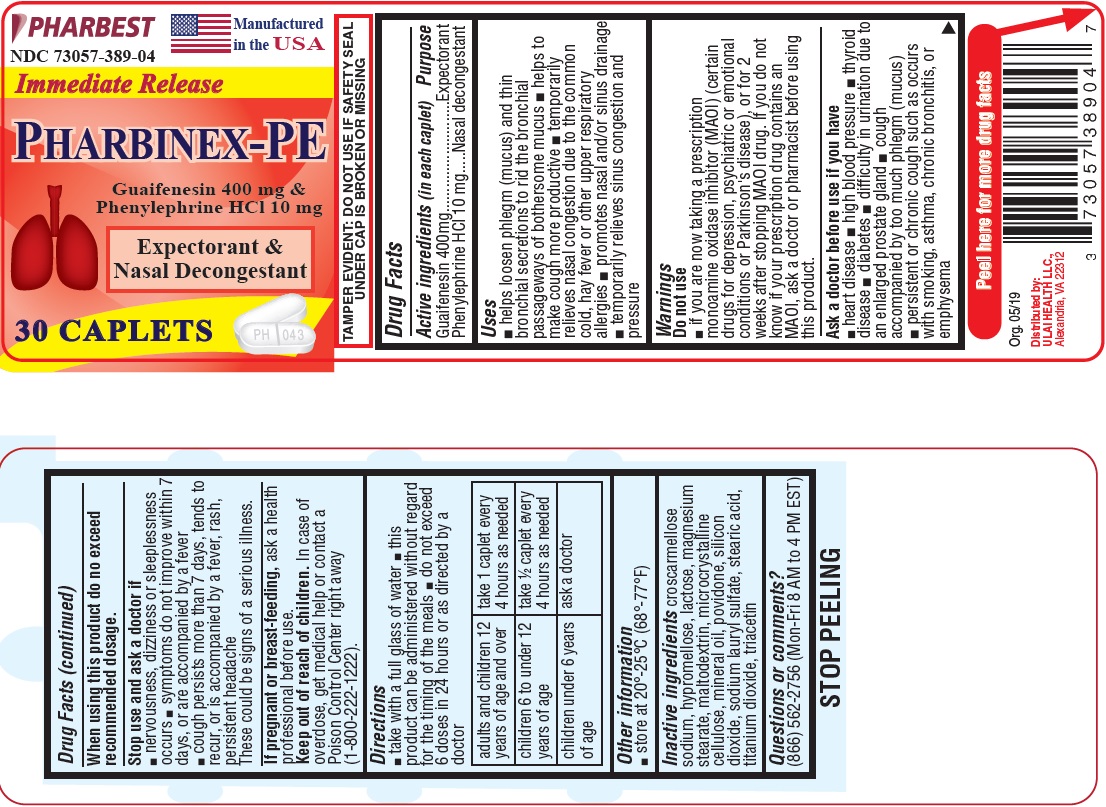 DRUG LABEL: Pharbinex-PE
NDC: 73057-389 | Form: TABLET, COATED
Manufacturer: Ulai Health LLC
Category: otc | Type: HUMAN OTC DRUG LABEL
Date: 20250120

ACTIVE INGREDIENTS: GUAIFENESIN 400 mg/1 1; PHENYLEPHRINE HYDROCHLORIDE 10 mg/1 1
INACTIVE INGREDIENTS: HYPROMELLOSE, UNSPECIFIED; LACTOSE MONOHYDRATE; MAGNESIUM STEARATE; MALTODEXTRIN; CELLULOSE, MICROCRYSTALLINE; MINERAL OIL; POVIDONE K30; POVIDONE K90; SILICON DIOXIDE; SODIUM LAURYL SULFATE; STEARIC ACID; TITANIUM DIOXIDE; CROSCARMELLOSE SODIUM; TRIACETIN

Drug Facts

Active ingredients (in each caplet)

Guaifenesin 400mg

Phenylephrine HCl 10mg

Purpose

Expectorant

Nasal decongestant

Uses

- helps loosen phlegm (mucus) and thin bronchial secretions to rid the bronchial passageways of bothersome mucus
- helps to make cough more productive
- temporarily relieves nasal congestion due to the common cold, hay fever or other upper respiratory allergies
- promotes nasal and/or sinus drainage
- temporarily relieves sinus congestion and pressure

Do not use

- if you are now taking a prescription monoamine oxidase inhibitor (MAOI) (certain drugs for depression, psychiatric or emotional conditions, or Parkinson’s disease), or for 2 weeks after stopping the MAOI drug. If you do not know if your prescription drug contains an MAOI, ask a doctor or pharmacist before taking this product.

Ask a doctor before use if you have

- heart disease
- high blood pressure
- thyroid disease
- diabetes
- difficulty in urination due to an enlarged prostate gland
- cough accompanied by too much phlegm (mucus)
- persistent or chronic cough such as occurs with smoking, asthma, chronic bronchitis, or emphysema

When using this product do not exceed recommended dosage.

Stop use and ask a doctor if

- nervousness, dizziness or sleeplessness occurs
- symptoms do not improve within 7 days, or are accompanied by a fever
- cough persists more than 7 days, tends to recur, or is accompanied by a fever, rash, persistent headache

These could be sings of a serious illness.

If pregnant or breast-feeding,

ask a health professional before use.

Keep out of reach of children.

In case of overdose, get medical help or contact a Poison Control Center right away (1-800-222-1222).

Directions

- take with a full glass of water
- this product can be administered without regard for the timing of the meals
- do not exceed 6 doses in 24 hours or as directed by a doctor

adults and children 12 years of age and over | take 1 caplet every 4 hours as needed
children 6 to under 12 years of age | take ½ caplet every 4 hours as needed
children under 6 years of age | ask a doctor

Other information

store at 20^0- 25^0C (68^0-77^0F)

Inactive ingredients

croscarmellose sodium, hypromellose, lactose, magnesium stearate, maltodextrin, microcrystalline celluclose, mineral oil, povidone, silicon dioxide, sodium lauryl sulfate, stearic acid, titanium dioxide, triacetin

Questions or comments?

(866) 562-2756 (Mon-Fri 8 AM to 4 PM EST)

TAMPER EVIDENT: DO NOT USE IF SAFETY SEAL UNDER CAP IS BROKEN OR MISSING

Distributed by:

ULAI HEALTH LLC.

Alexandria, VA 22312

PACKAGE LABEL

PHARBEST

NDC 73057-389-04

Manufactured in the USA

Immediate Release

PHARBINEX-PE

Guaifenesin 400mg

Phenylephrine HCl 10mg

Expectorant &

Nasal Decongestant

30 CAPLETS